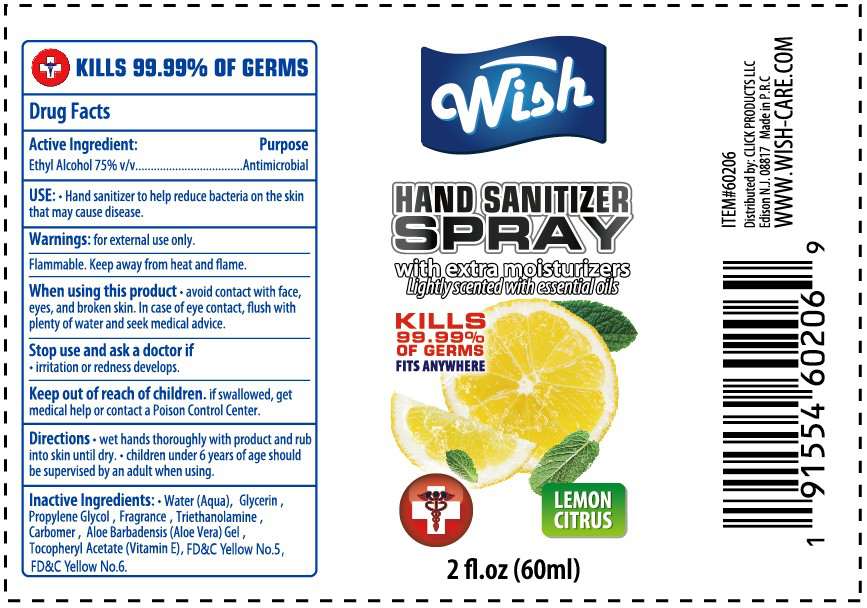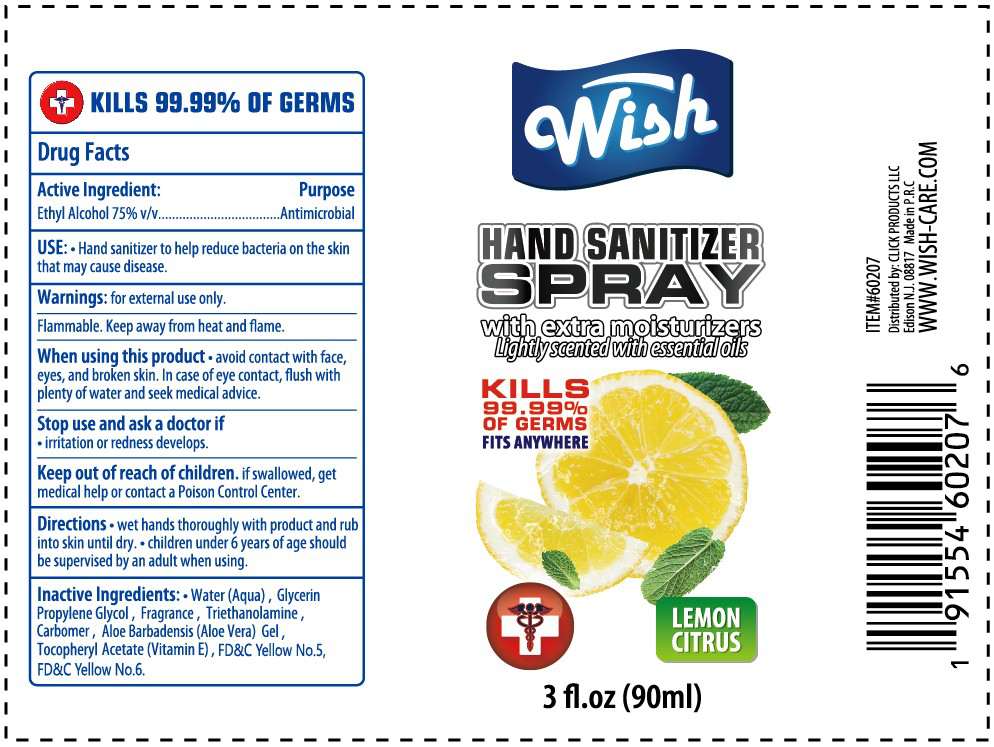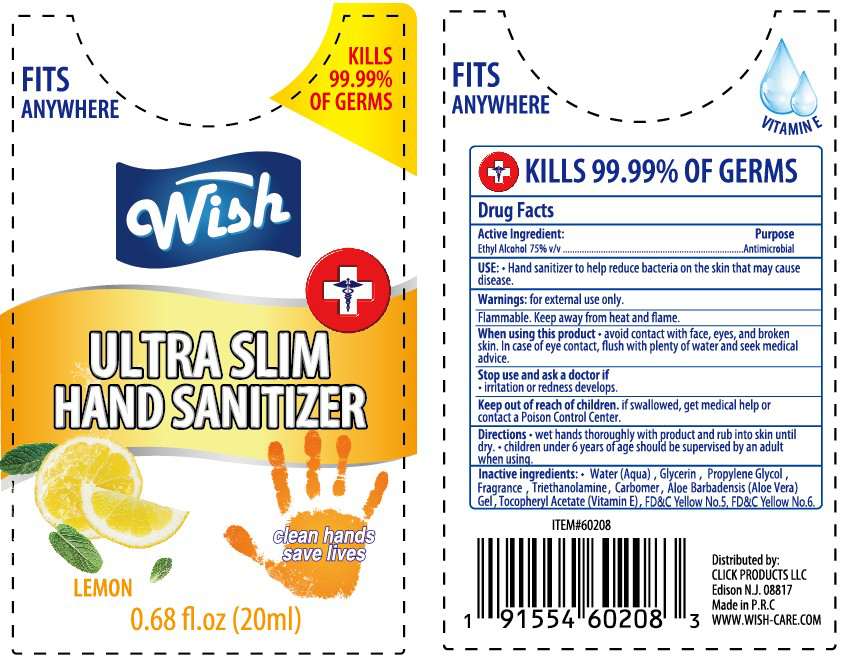 DRUG LABEL: Wish Ultra slim hand sanitizer
NDC: 71611-031 | Form: LIQUID
Manufacturer: Click Products LLC
Category: otc | Type: HUMAN OTC DRUG LABEL
Date: 20200604

ACTIVE INGREDIENTS: ALCOHOL 70.4 mL/100 mL
INACTIVE INGREDIENTS: FD&C YELLOW NO. 6 0.00005 mL/100 mL; FD&C YELLOW NO. 5 0.00015 mL/100 mL; CARBOMER 940 0.1 mL/100 mL; GLYCERIN 0.5 mL/100 mL; PROPYLENE GLYCOL 0.5 mL/100 mL; TROLAMINE 0.1 mL/100 mL; .ALPHA.-TOCOPHEROL ACETATE 0.05 mL/100 mL; ALOE VERA LEAF 0.05 mL/100 mL; WATER 28.0998 mL/100 mL; LEMON JUICE 0.2 mL/100 mL

hand sanitizer -60206-2/60207-2/ 60208-3

Hand Sanitizer

Kills 99.9% of germs

Active ingredient

Active Ingredient Purpose

Ethyl Alcohol 75% v/v Antimicrobial

use

Reduce bacteria and viruses onthe hands that may cause disease.

Warning

for external use only.

Flammable

Keep away from heat and flame.

When using this product

Avoid contact with face, eyes and broken skin. In case of eye contact, flush with plenty of water and seek medical advice.

Stop and ask a doctor if

irritation or redness develops.

Keep out of reach of children.

If swallowed get immediate medical help or contact a poison contaol center right away.

Directions

DOSAGE AND ADMINISTRATION

Wet hands thoroughly with product and rub into skin until dry.

USER SAFETY WARNINGS

Children under 6 years of age should be supervised by an adult when using.

Inactive Ingredients:

Water(aqua), Glycerin, Propylene Glycol, Carbomer, Triethanolamine, Fragrance, Aloe Barbadensis(Aloe Vera) Gel, Tocopheryl acetate(vitamin E), FD&C Yellow No. 5, FD&C Yellow No. 6.